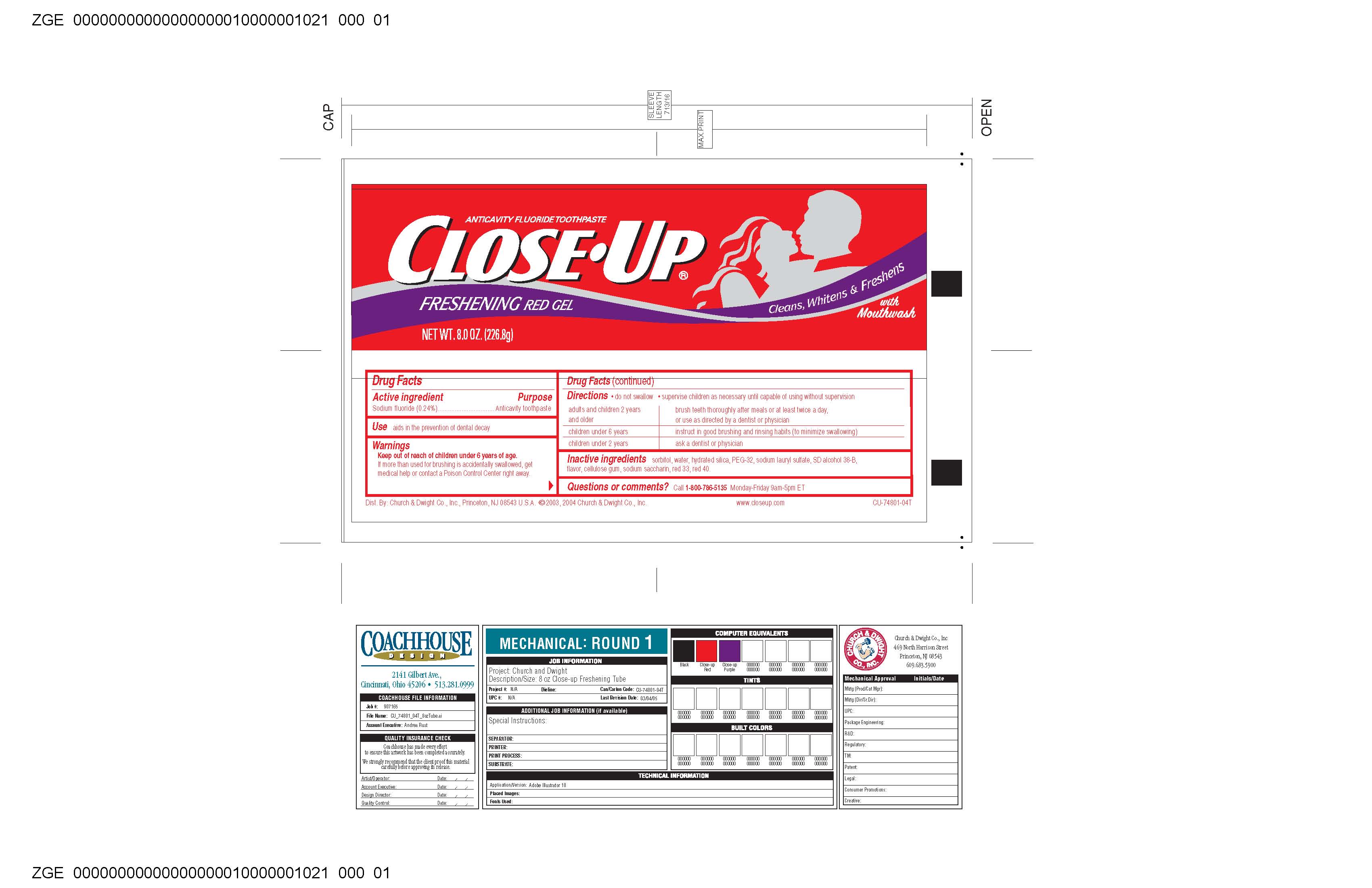 DRUG LABEL: Close Up Anticavity Toothpaste
NDC: 61047-771 | Form: GEL
Manufacturer: KIK Custom Products
Category: otc | Type: HUMAN OTC DRUG LABEL
Date: 20100326

ACTIVE INGREDIENTS: Sodium Fluoride 0.54 g/226.8 g

Close Up Anticavity Fluoride Toothpaste

Drug Facts:
Sodium Fluoride: 0.24%
Purpose: Anticavity Toothpaste

KEEP OUT OF REACH OF CHILDREN UNDER 6 YEARS OF AGE.

IF MORE THAN USED FOR BRUSHING, IS ACCIDENTALLY SWALLOWED. GET MEDICAL HELP OR CONTACT A POISON CONTROL CENTER RIGHT AWAY.

INACTIVE INGREDIENT

Sorbitol , Water, Hydrated Silica, PEG-32, Sodium Lauryl Sulfate, SD-Alcohol 38B, Flavor, Cellulose Gum, Sodium Saccharin, Red33, Red40

Questions or Comments ?: Call 1-800-786-5135 Monday -Friday 9am-5pmET